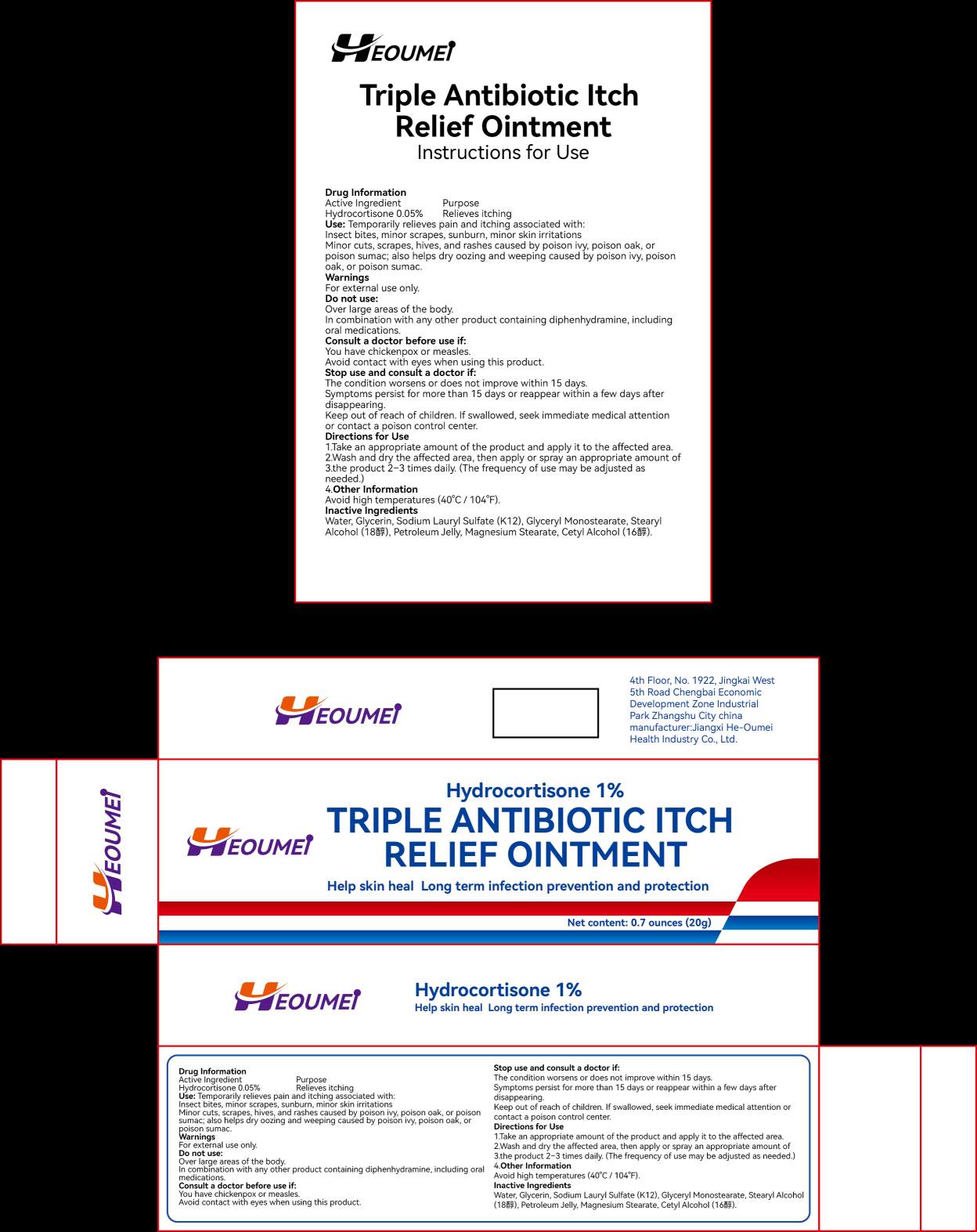 DRUG LABEL: Triple Antibiotic
NDC: 87365-473 | Form: CREAM
Manufacturer: Jiangxi He-Oumei Health Industry Co., Ltd.
Category: homeopathic | Type: HUMAN OTC DRUG LABEL
Date: 20260124

ACTIVE INGREDIENTS: HYDROCORTISONE 1 g/1 1
INACTIVE INGREDIENTS: METHOXY PEG-22/DODECYL GLYCOL COPOLYMER; STEARYL ALCOHOL; GLYCERYL MONOSTEARATE; WATER

ACTIVE INGREDIENT

Hydrocortisone

PURPOSE

Anti-inflammatory

keep out of reach of children section

keep out of reach of children section

INACTIVE INGREDIENT

Glyceryl Monostearate,Stearyl Alcohol,Water,Vaseline

INDICATIONS AND USAGE

Anti-inflammatory

DOSAGE AND ADMINISTRATION

Apply to the affected area